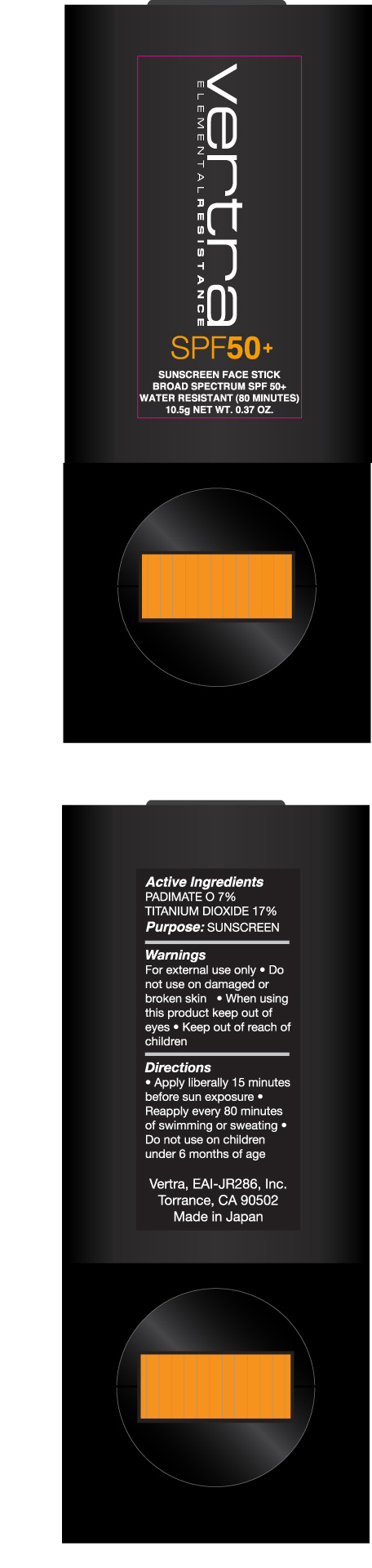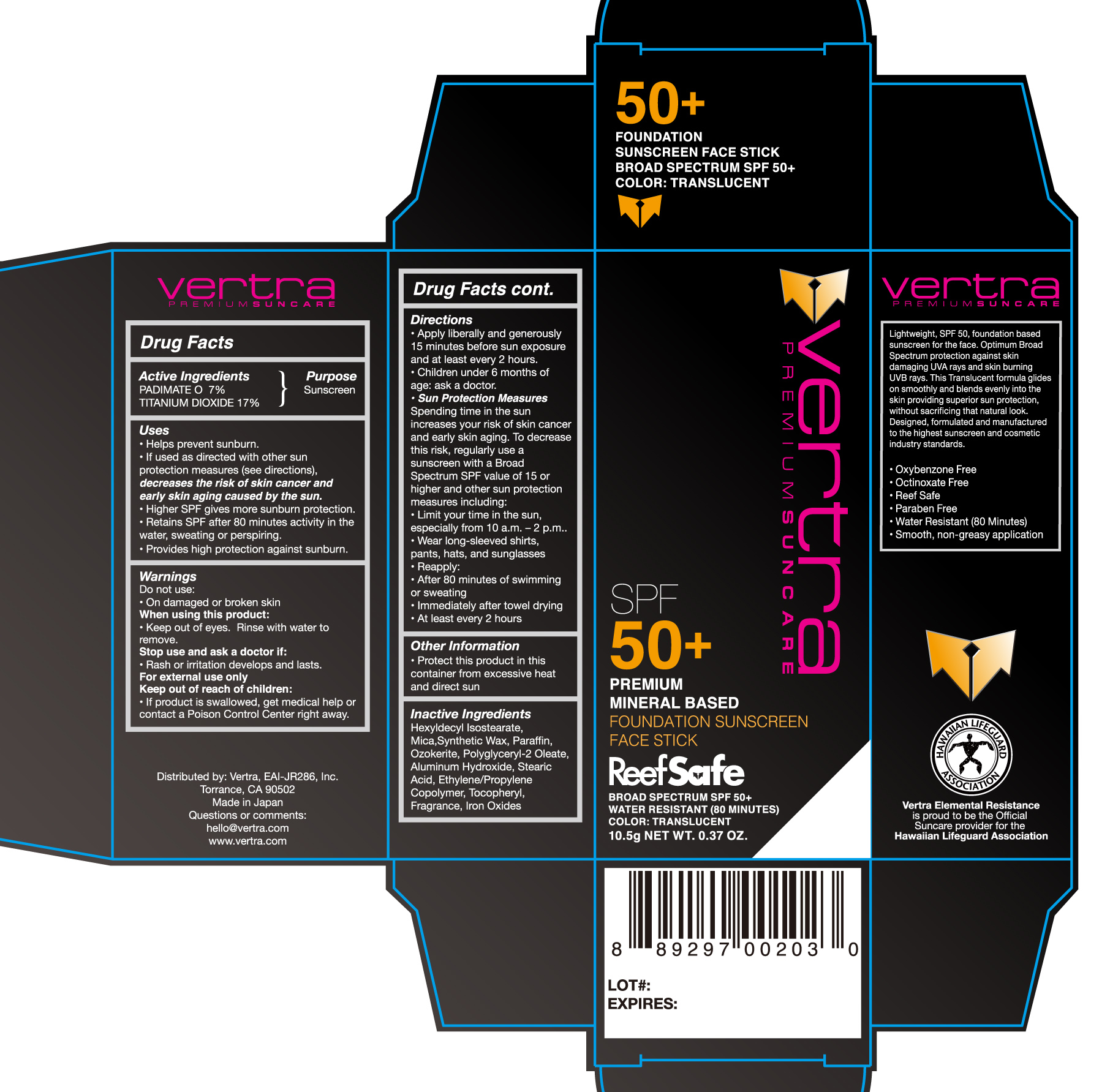 DRUG LABEL: Translucent Broad Spectrum Foundation SPF 50
NDC: 71014-005 | Form: STICK
Manufacturer: Eai-Jr286, Inc.
Category: otc | Type: HUMAN OTC DRUG LABEL
Date: 20200108

ACTIVE INGREDIENTS: PADIMATE O 7 g/100 g; TITANIUM DIOXIDE 17.45 g/100 g
INACTIVE INGREDIENTS: ALUMINUM HYDROXIDE; HEXYLDECYL ISOSTEARATE; MICA; CERESIN; PARAFFIN; STEARIC ACID; SYNTHETIC WAX (1200 MW); TOCOPHEROL

Vertra Elemental Resistance Broad Spectrum Foundation Face Screen SPF 50 - Translucent

Active Ingredients Purpose

Padamite O 7% Sunscreen

Titanium Dioxide 17%

Uses

- helps prevent sunburn
- if used as directed with other sun protection measures (see Directions), decreases the risk of skin cancer and early skin aging caused by the sun
- Higher SPF gives more sunburn protection
- Retains SPF after 80 minutes activity in the water, sweating, or perspiring
- Provides high protection against sunburn

Keep out of reach of children. If products is swallowed, get medical help or contact Poison Control Center right away.

Stop use and ask a doctor if rash or irritation develops and lasts

Warnings

For external use only

- Do not use on damaged or broken skin
- When using this product keep out of eyes
- Rinse with water to remove

Directions

- apply liberally and evenly 15 minutes before sun exposure
- apply to all skin exposed to sun
- use a water resistant sunscreen if swimming or sweating
- reapply: after 80 minutes of swimming or sweating
- immeadiately after towel drying
- at least every 2 hours
- Sun Protection Measures. Spending time in the sun increases your risk of skin cancer and early skin aging. To decrease this risk, regularly use a sunscreen with a Broad Spectrum SPF value of 15 or higher and otther sun protection measures including:
- limit time in the sun, especially from 10 a.m. - 2 p.m.
- wear long-sleeve shirts, pants, hats, and sunglasses
- children under 6 months of age: ask a doctor

INACTIVE INGREDIENT

Hexyldecyl Isosterate, Mica, Synthetic wax, Paraffin, Ozokerite, Polyglyceryl-2 Oleate, Aluminum Hydroxide, Stearic Acid, Ethylene/Propylene Copolymer, Tocopheryl, Fragrance, Iron Oxides

PACKAGE LABEL

Vertra Elemental Resistance

Foundation

Sunscreen Face Stick

Broad Spectrum SPF 50+

Water Resistant (80 minutes)

Color: Translucent

10.5g NET WT. .37 oz.